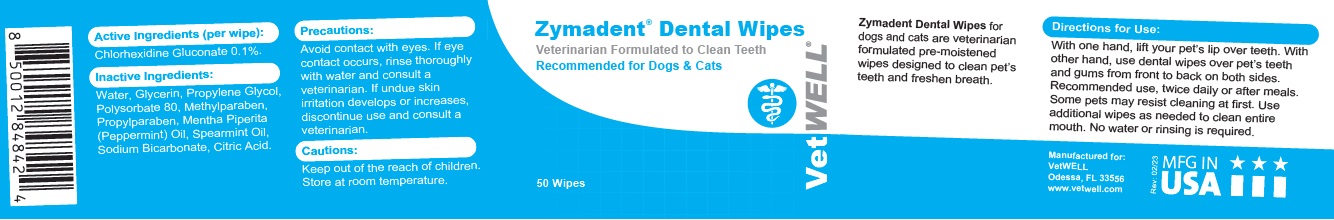 DRUG LABEL: Zymadent Dental Wipes
NDC: 86090-009 | Form: CLOTH
Manufacturer: Pet MD Brands, LLC
Category: animal | Type: OTC ANIMAL DRUG LABEL
Date: 20230907

ACTIVE INGREDIENTS: CHLORHEXIDINE GLUCONATE 0.1 g/100 g
INACTIVE INGREDIENTS: WATER; GLYCERIN; PROPYLENE GLYCOL; POLYSORBATE 80; METHYLPARABEN; PROPYLPARABEN; PEPPERMINT OIL; SPEARMINT OIL; SODIUM BICARBONATE; CITRIC ACID MONOHYDRATE

Zymadent® Dental Wipes

Active Ingredients (per wipe):

Chlorhexidine Gluconate 0.1%.

INDICATIONS AND USAGE

Zymadent Dental Wipes for dogs and cats are veterinarian formulated pre-moistened wipes designed to clean pet’s teeth and freshen breath.

Inactive Ingredients:

Water, Glycerin, Propylene Glycol, Polysorbate 80, Methylparaben, Propylparaben, Mentha Piperita (Peppermint) Oil, Spearmint Oil, Sodium Bicarbonate, Citric Acid.

Precautions:

Avoid contact with eyes. If eye contact occurs, rinse thoroughly with water and consult a veterinarian. If undue skin irritation develops or increases, discontinue use and consult a veterinarian.

Cautions:

Keep out of the reach of children.

STORAGE AND HANDLING

Store at room temperature.

Directions for Use:

With one hand, lift your pet’s lip over teeth. With other hand, use dental wipes over pet’s teeth and gums from front to back on both sides. Recommended use, twice daily or after meals. Some pets may resist cleaning at first. Use additional wipes as needed to clean entire mouth. No water or rinsing is required.

Veterinarian Formulated to Clean Teeth

Recommended for Dogs & Cats

Manufactured for:
VetWELL
Odessa, FL 33556
www.vetwell.com

MFG IN USA